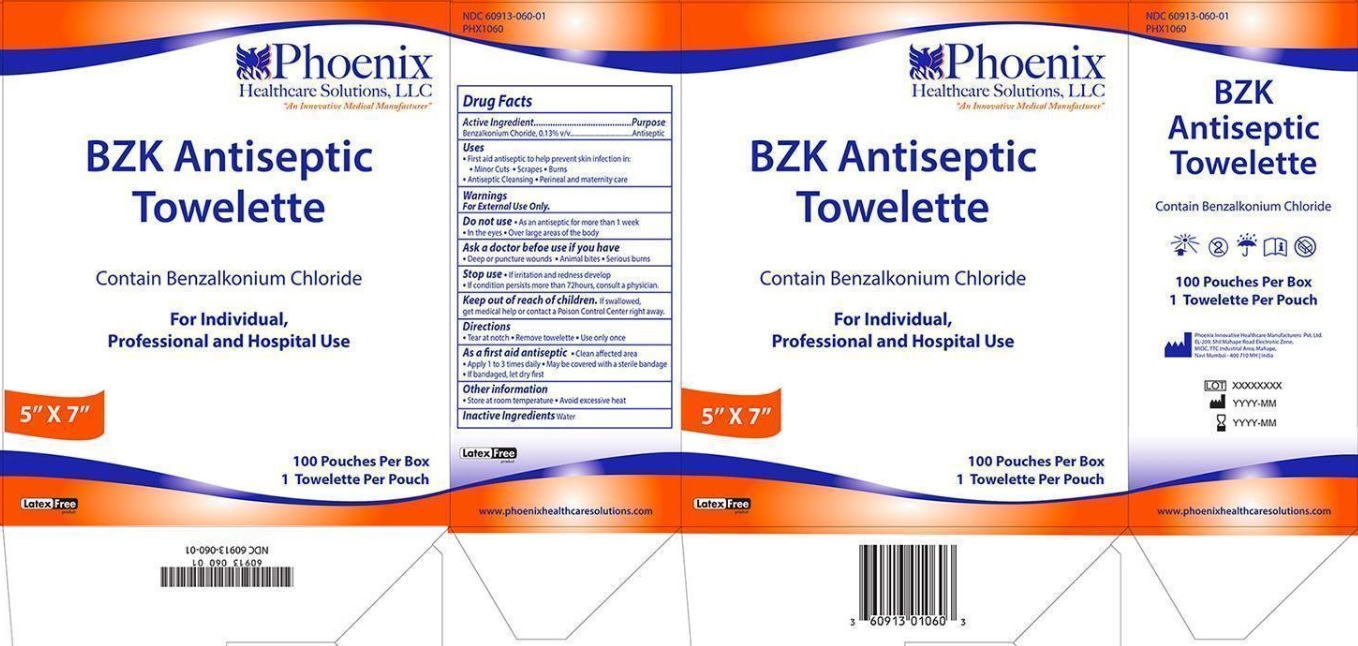 DRUG LABEL: BZK Antiseptic
NDC: 60913-060 | Form: SOLUTION
Manufacturer: PHOENIX HEALTHCARE SOLUTIONS, LLC
Category: otc | Type: HUMAN OTC DRUG LABEL
Date: 20251023

ACTIVE INGREDIENTS: BENZALKONIUM CHLORIDE 0.13 g/100 g
INACTIVE INGREDIENTS: WATER

Granex BZK Antiseptic Towelette

Active ingredient

Benzalkonium Chloride, 0.13% v/v

Purpose

Antiseptic

Uses

- First aid antiseptic to help prevent skin infection in: minor cuts, scrapes and burns
- Antiseptic Cleansing
- Perineal and maternity care

Warnings:

For external use only

Do not

- As an antiseptic for more than 1 week
- In the eyes
- Over large areas of the body

Ask a doctor before use if you have

- Deep or puncture wounds
- Animal bites
- Serious burns

Stop use

- If irritation and redness develop
- If condition persists more than 72 hours, consult a physician.

Keep out of reach of children

If swallowed, get medical help or contact a Poison Control Center right away.

Directions:

- Tear at notch
- Remove towelette
- Use only once

As a first aid antiseptic:

- Clean affected area
- Apply 1 to 3 times daily
- May be covered with a sterile bandage
- If bandaged, let dry first

Other information

- Store at room temperature
- Avoid excessive heat

Inactive ingredients:

Water

Principal Display Panel

NDC 60913-060-01

Phoenix Healthcare Solutions LLC

"An Innovative Medical Manufacturer"

BZK Antiseptic Towelette

Contains Benzalkonium Chloride

For Individual, Professional and Hospital Use

100 Pouches Per Box

1 Towelette Per Pouch